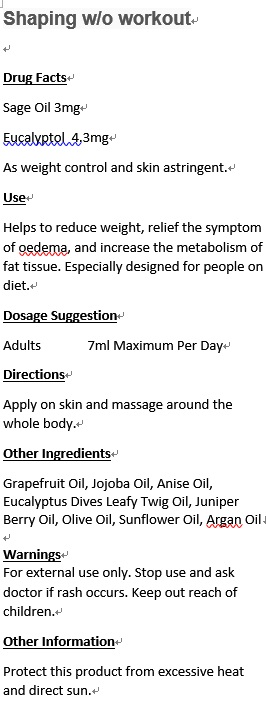 DRUG LABEL: Menopause Care Synergy
NDC: 70470-1809 | Form: OIL
Manufacturer: PHYTOPIA CO., LTD.
Category: otc | Type: HUMAN OTC DRUG LABEL
Date: 20161024

ACTIVE INGREDIENTS: SAGE OIL 3 mg/50 mL
INACTIVE INGREDIENTS: CURCUMA ZEDOARIA LEAF; TURMERIC OIL; JASMINUM OFFICINALE FLOWER; ANISE OIL; CITRUS RETICULATA LEAF OIL; ROSA CENTIFOLIA FLOWER OIL; JOJOBA OIL; OLIVE OIL; SUNFLOWER OIL; EVENING PRIMROSE OIL; GERANIUM OIL, ALGERIAN TYPE

Drug Facts

Sage Oil 3mg

Eucalyptol 4.3mg

As Weight Control And Skin Astringent.

Use

Helps to reduce weight, relief the symptom of oedema, and increase the metabolism of fat tissue. Especially designed for people on diet.

Dosage Suggestion

Adults 7ml Maximum Per Day

Directions

Apply on skin and massage around the whole body.

INACTIVE INGREDIENT

Other Ingredients

Grapefruit Oil, Jojoba Oil, Anise Oil, Eucalyptus Dives Leafy Twig Oil, Juniper Berry Oil, Olive Oil, Sunflower Oil, Argan Oil

Warnings

For external use only. Stop use and ask doctor if rash occurs. Keep out of reach of children.

Warnings

For external use only. Stop use and ask doctor if rash occurs. Keep out of reach of children.

Other Information

Protect this product from excessive heat and direct sun.

PACKAGE LABEL

Shaping w/o Workout